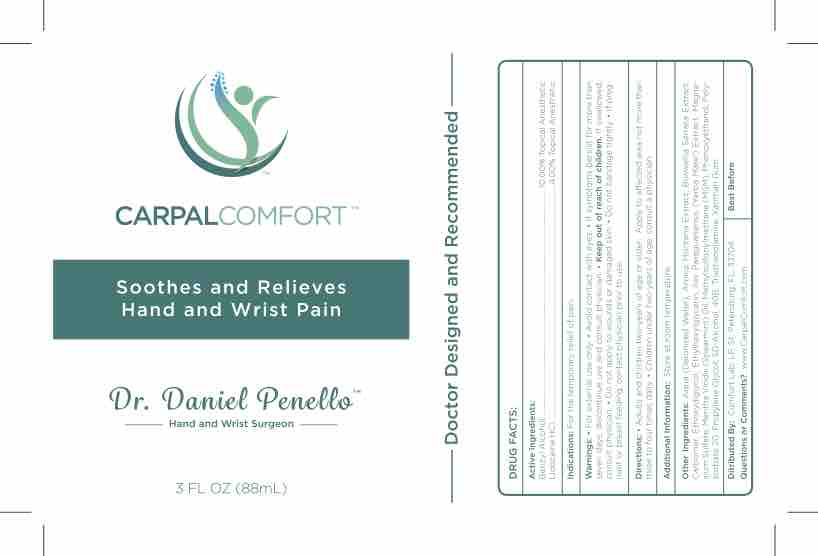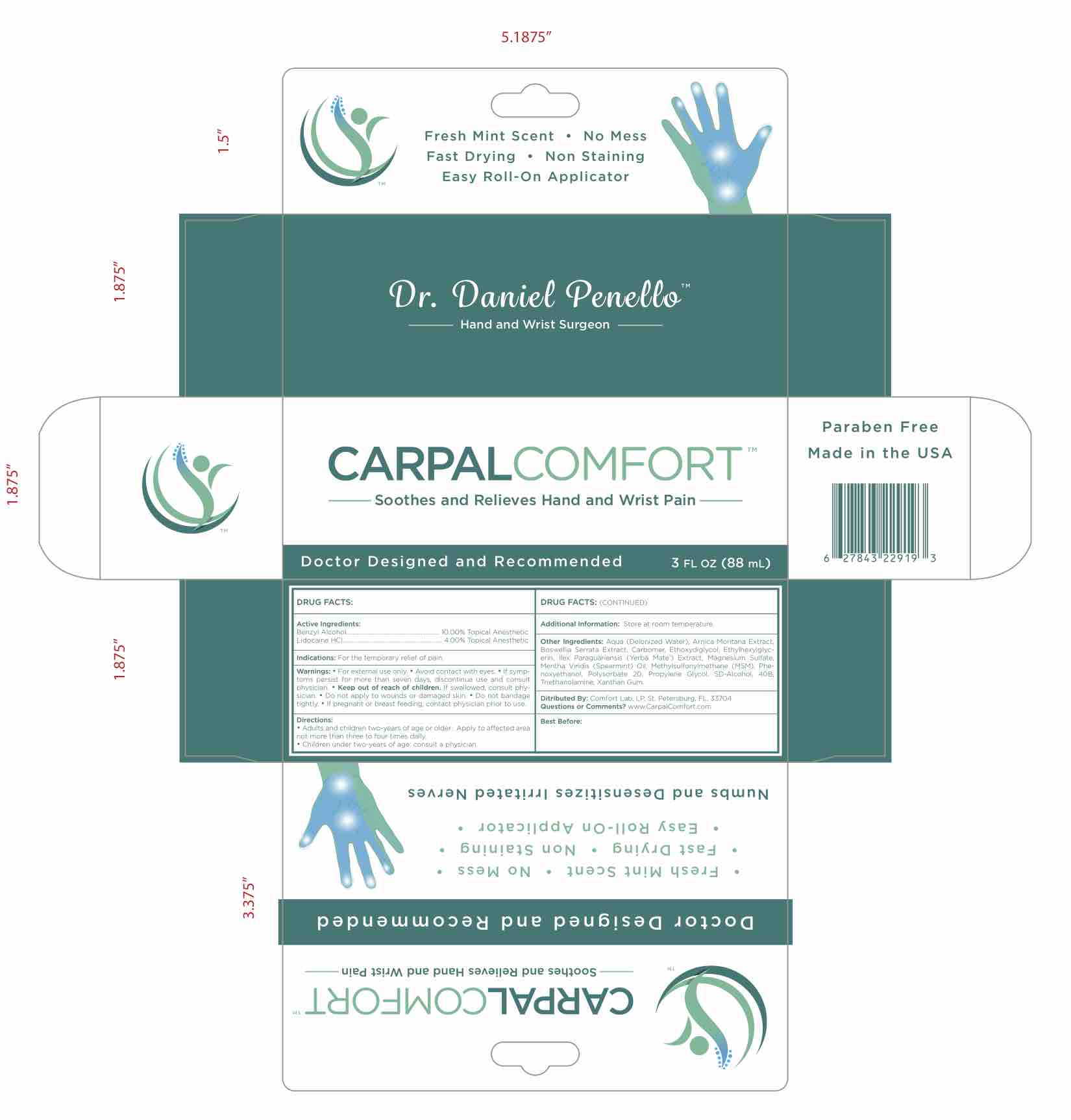 DRUG LABEL: Carpal Comfort
NDC: 73214-001 | Form: CREAM
Manufacturer: Comfort Lab, LP
Category: otc | Type: HUMAN OTC DRUG LABEL
Date: 20230110

ACTIVE INGREDIENTS: BENZYL ALCOHOL 10 mg/100 mL; LIDOCAINE HYDROCHLORIDE 4 mg/100 mL
INACTIVE INGREDIENTS: ETHOXYDIGLYCOL BEHENATE; DIMETHYL SULFONE; POLYSORBATE 20; PROPYLENE GLYCOL; BOSWELLIA SERRATA RESIN OIL; ILEX PARAGUARIENSIS LEAF; MAGNESIUM SULFATE, UNSPECIFIED; SPEARMINT OIL; ALCOHOL; TRIETHANOLAMINE SULFATE; XANTHAN GUM; WATER; PHENOXYETHANOL; ARNICA MONTANA FLOWER WATER; CARBOMER 940

Carpal Comfort

ACTIVE INGREDIENT

Benzyl Alcohol, Lidocaine HCl

INDICATIONS

For temporary relief of pain.

WARNINGS

- For external use only
- Avoid contact with eyes

Keep out of reach of children. If swallowed, consult physician.

PREGNANCY OR BREAST FEEDING

If pregnant or breast feeding, contact physician prior to use.

STOP USE

If symptoms persist more than seven days, discontinue use and consult physician.

ADDITIONAL INFORMATION

Store at room temperature.

Questions or comments? www.carpalcomfort.com

PURPOSE

Topical Anesthetic

INDICATIONS AND USAGE

LIDOCAINE HYDROCHLORIDE

BENZYL ALCOHOL

POLYSORBATE 20

PROPYLENE GLYCOL

BOSWELLIA SERRATA RESIN OIL

ILEX PARAGUARIENSIS LEAF

MAGNESIUM SULFATE, UNSPECIFIED

SPEARMINT OIL

ALCOHOL

TRIETHANOLAMINE SULFATE

XANTHAN GUM

WATER

PHENOXYETHANOL

ARNICA MONTANA FLOWER WATER

DIMETHYL SULFONE

CARBOMER 980

ETHOXYDIGLYCOL BEHENATE

DOSAGE AND ADMINISTRATION

Adults and children two-years of age and older:

Apply to affected area not more than three to four times a day.

Children under two years of age:

Consult a physician

INACTIVE INGREDIENT

LIDOCAINE HYDROCHLORIDE

BENZYL ALCOHOL

POLYSORBATE 20

PROPYLENE GLYCOL

BOSWELLIA SERRATA RESIN OIL

ILEX PARAGUARIENSIS LEAF

MAGNESIUM SULFATE, UNSPECIFIED

SPEARMINT OIL

ALCOHOL

TRIETHANOLAMINE SULFATE

XANTHAN GUM

WATER

PHENOXYETHANOL

ARNICA MONTANA FLOWER WATER

DIMETHYL SULFONE

CARBOMER 980

ETHOXYDIGLYCOL BEHENATE